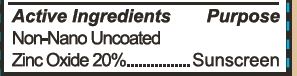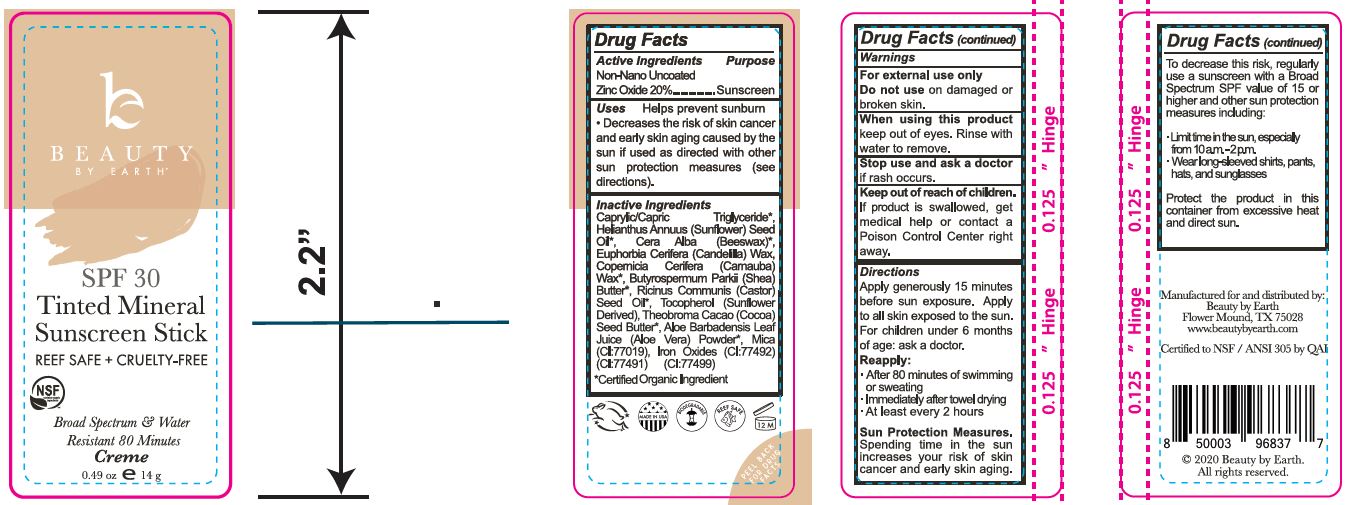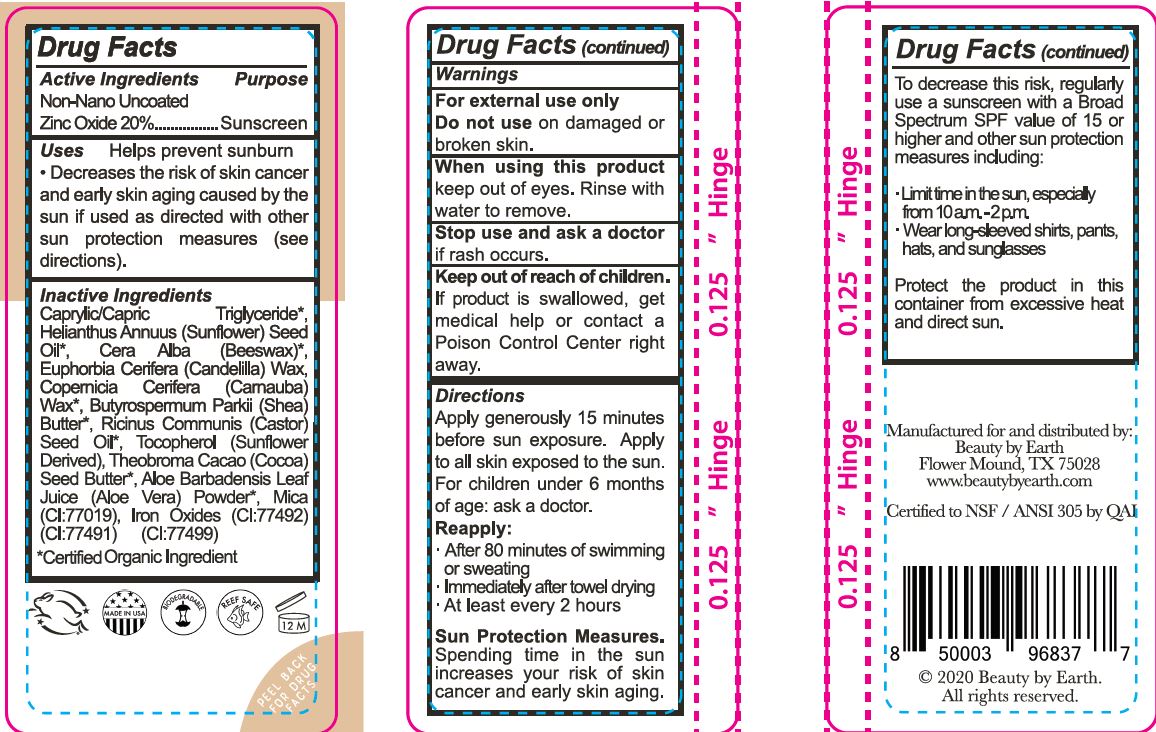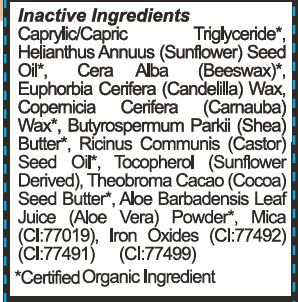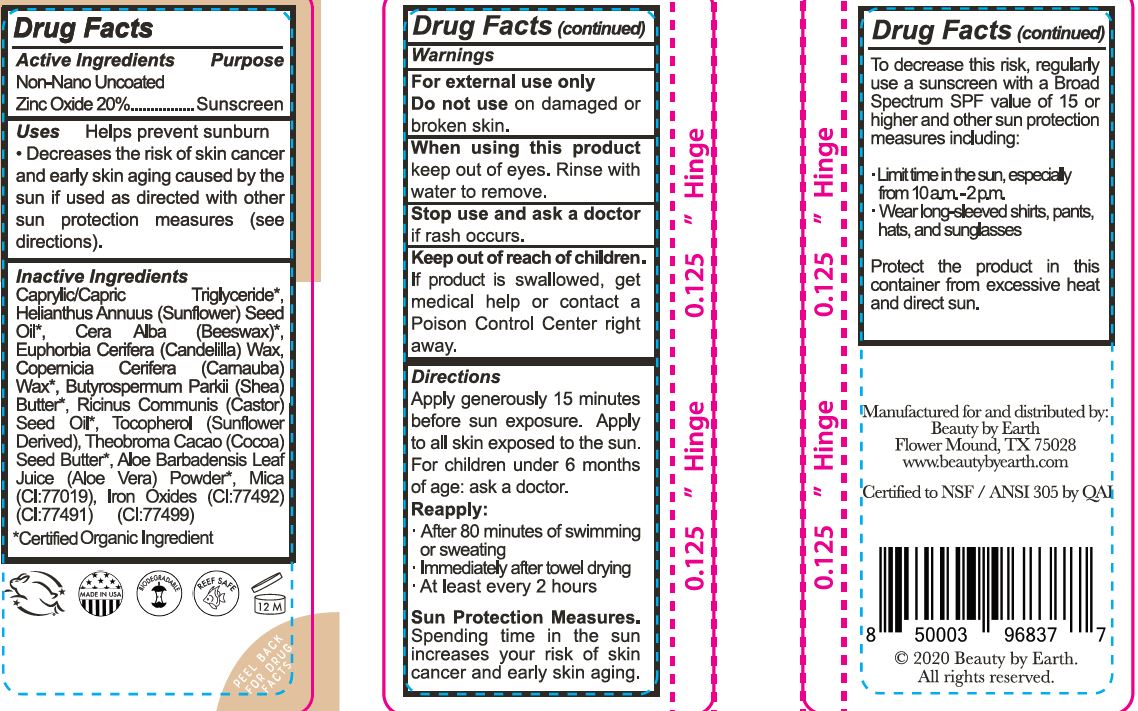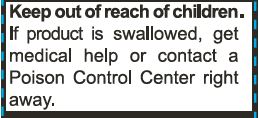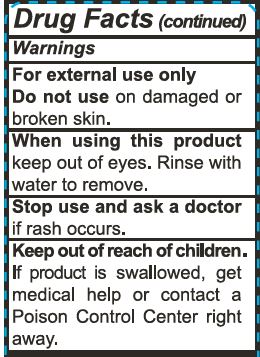 DRUG LABEL: Tinted Mineral Face Sunscreen Stick - Creme
NDC: 62932-221 | Form: STICK
Manufacturer: Private Label Select Ltd CO
Category: otc | Type: HUMAN OTC DRUG LABEL
Date: 20201228

ACTIVE INGREDIENTS: ZINC OXIDE 20 g/100 g
INACTIVE INGREDIENTS: ALOE VERA LEAF; CASTOR OIL; FERRIC OXIDE RED; CARNAUBA WAX; .ALPHA.-TOCOPHEROL, D-; .BETA.-TOCOPHEROL; SUNFLOWER OIL; CANDELILLA WAX; SHEA BUTTER; FERROSOFERRIC OXIDE; COCOA BUTTER; WHITE WAX; MICA; MEDIUM-CHAIN TRIGLYCERIDES; FERRIC OXYHYDROXIDE; .GAMMA.-TOCOPHEROL; .DELTA.-TOCOPHEROL

Beauty By Earth Tinted Mineral Face Sunscreen Stick - Creme